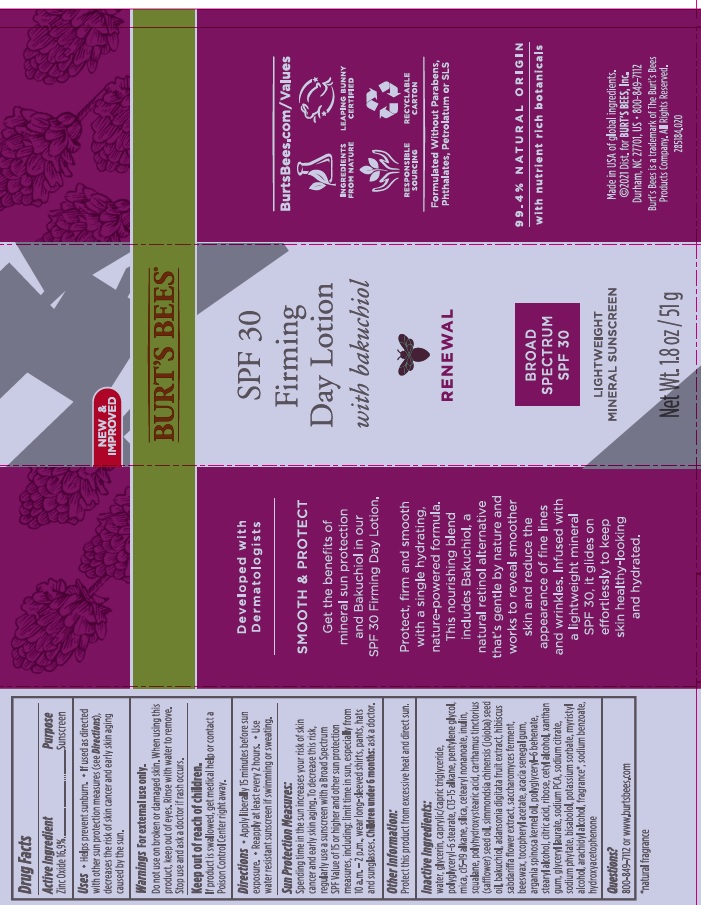 DRUG LABEL: Burts Bees Firming Day
NDC: 26052-493 | Form: LOTION
Manufacturer: Burts Bees
Category: otc | Type: HUMAN OTC DRUG LABEL
Date: 20241203

ACTIVE INGREDIENTS: ZINC OXIDE 16.9 g/100 g
INACTIVE INGREDIENTS: WATER; MEDIUM-CHAIN TRIGLYCERIDES; C13-15 ALKANE; PENTYLENE GLYCOL; MICA; C15-19 ALKANE; SILICON DIOXIDE; CETEARYL NONANOATE; INULIN; SQUALANE; SAFFLOWER OIL; CETOSTEARYL ALCOHOL; JOJOBA OIL; POLYHYDROXYSTEARIC ACID (2300 MW); ARGAN OIL; .ALPHA.-TOCOPHEROL ACETATE; CITRIC ACID MONOHYDRATE; HYDROXYACETOPHENONE; XANTHAN GUM; POLYGLYCERYL-6 BEHENATE; GLYCERYL LAURATE; SODIUM PYRROLIDONE CARBOXYLATE; YELLOW WAX; ACACIA; SODIUM CITRATE; HEXASODIUM PHYTATE; POTASSIUM SORBATE; HIBISCUS SABDARIFFA FLOWER; ADANSONIA DIGITATA FRUIT; BAKUCHIOL; RIBOSE, D-; LEVOMENOL; GLYCERIN; POLYGLYCERYL-6 STEARATE

Burt's Bees Firming Day Lotion SPF30

Active Ingredient

Zinc Oxide 16.9%

Purpose

Sunscreen

Uses

- Helps prevent sunburn
- If used as directed with other sun protection measures (see Directions), decreases the risk of skin cancer and early skin aging caused by the sun.

Warnings

For external use only.

Do not use on broken or damaged skin.

When using this product, keep out of eyes. Rinse with water to remove.

Stop use and ask a doctor if rash occurs.

Keep out of reach of children.

If product is swalloed, get medical help or contact a Poison Control Center right away.

Directions

- Apply liberally 15 minutes before sun exposure
- Reapply

Sun Protection Measures

Spending time in the sun increases your risk of skin cancer and early skin aging. To decrease this risk, regularly us a sunscreen with a Broad Spectrum SPF value of 15 or higher and other sun protection measures including: limit time in sun, especially from 10a.m.-2p.m., wear long-sleeved shirts, pants, hats and sunglasses . Children under 6 months: ask a doctor.

Other Information

Protect this product from excessive hear and direct sun.

Inactive Ingredients:

water, glycerin, caprylic/capric triglyceride, polyglyceryl-6 stearate, C13-15 alkane, pentylene glycol, mica, c15-19 alkane, silica, cetearyl nonanoate, inulin, squalane, carthamus tinctorius (safflower) seed oil, cetearyl alcohol, simmondsia chinensis (jojoba) seed oil, polyhydroxystearic acid, argania spinosa kernel oil, saccharomyces ferment filtrate, tocopheryl acetate, citric acid, hydroxyacetonphenone, ribosa, xanthan gum, polyglyceryl-6 behenate, glyceryl laurate, sodium PCA, beeswax, acacia senegal gum, bakuchiol, fragrance, sodium citrate, c12-26 alkane, sodium phytate, bisabolol, potassium sorbate, adansonia digitata fruit extract, hibiscus sabdariffa flower extract.